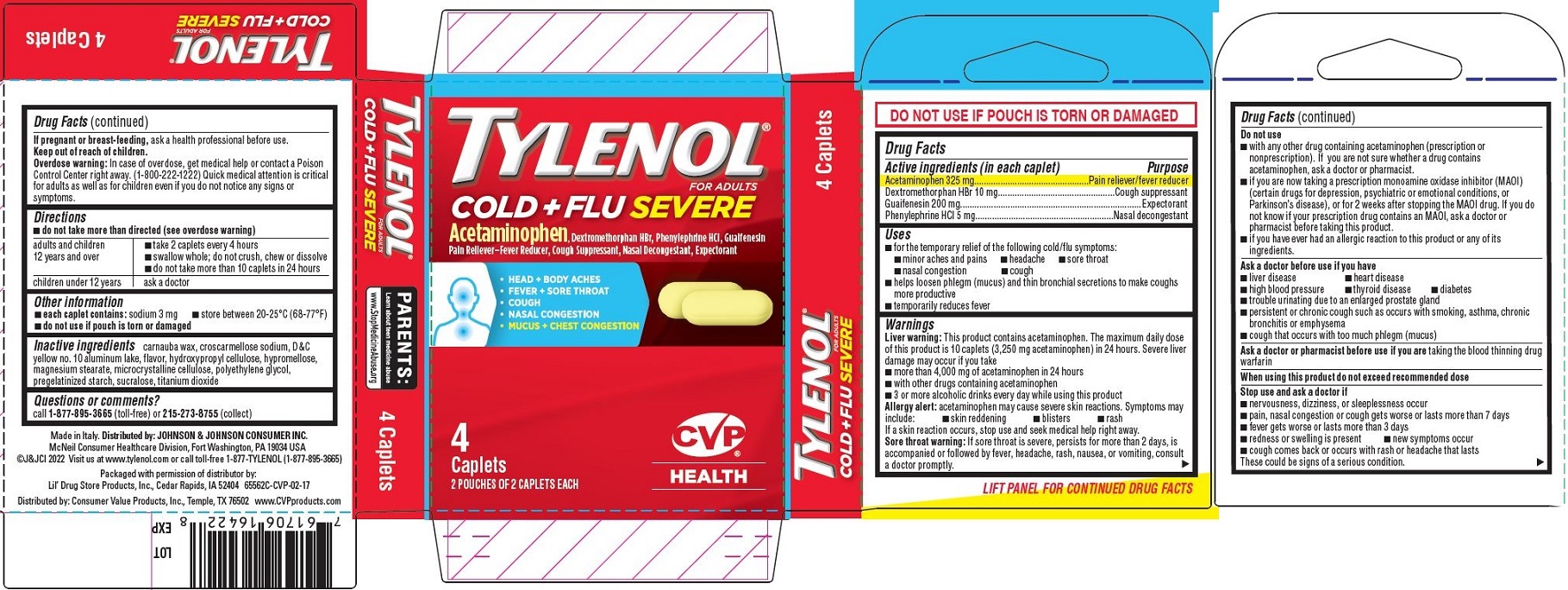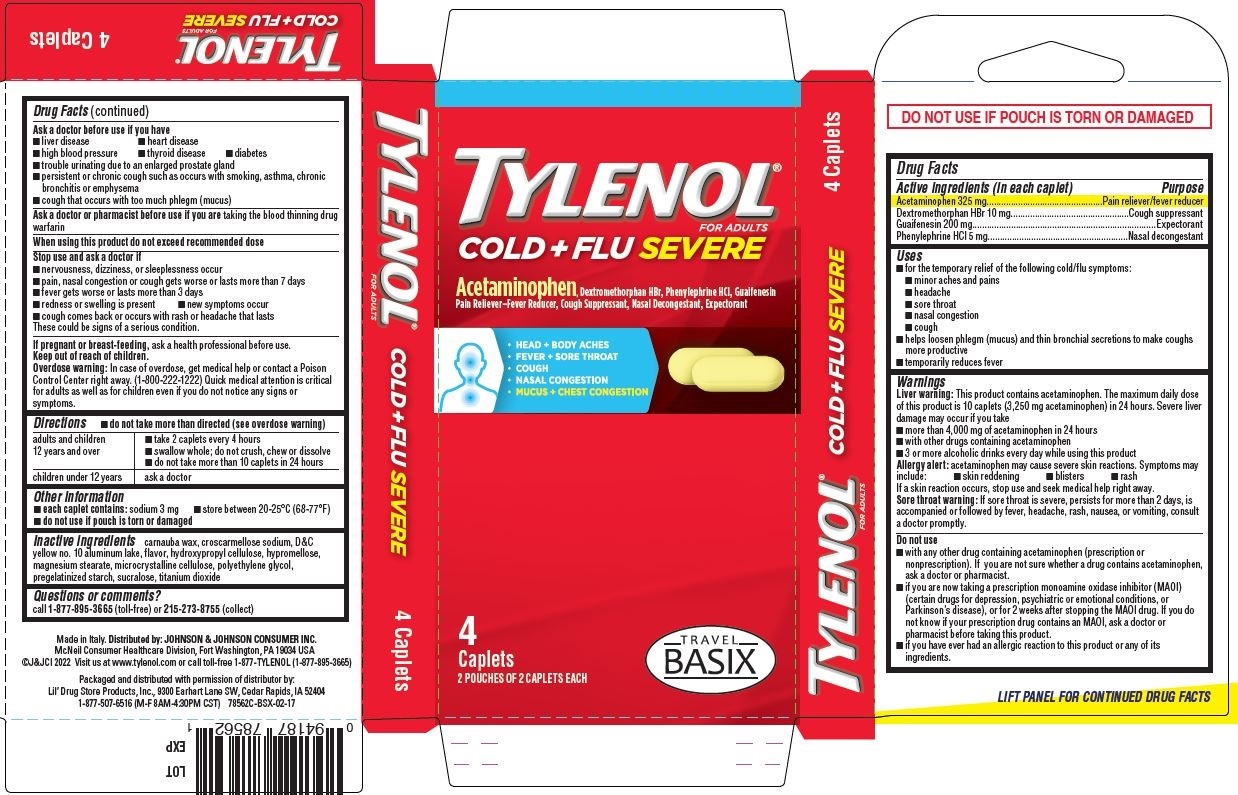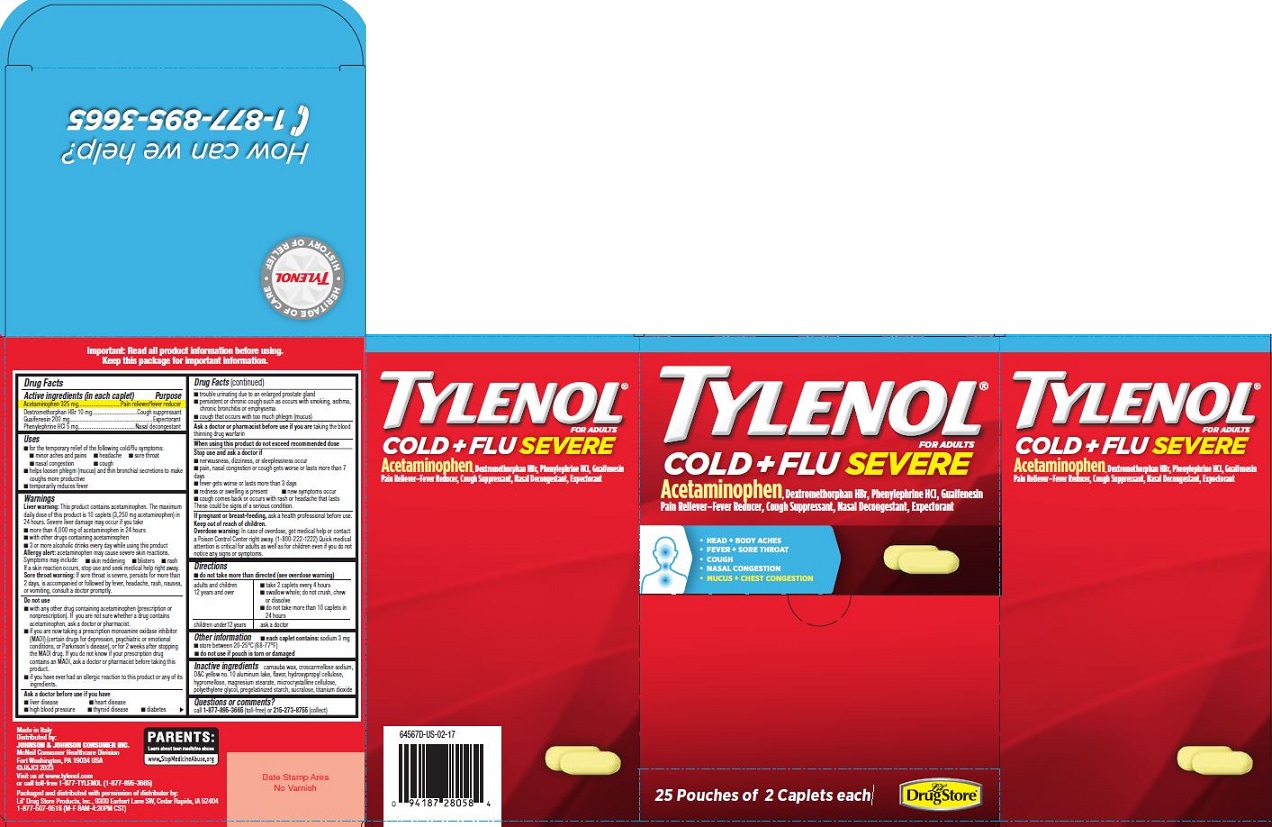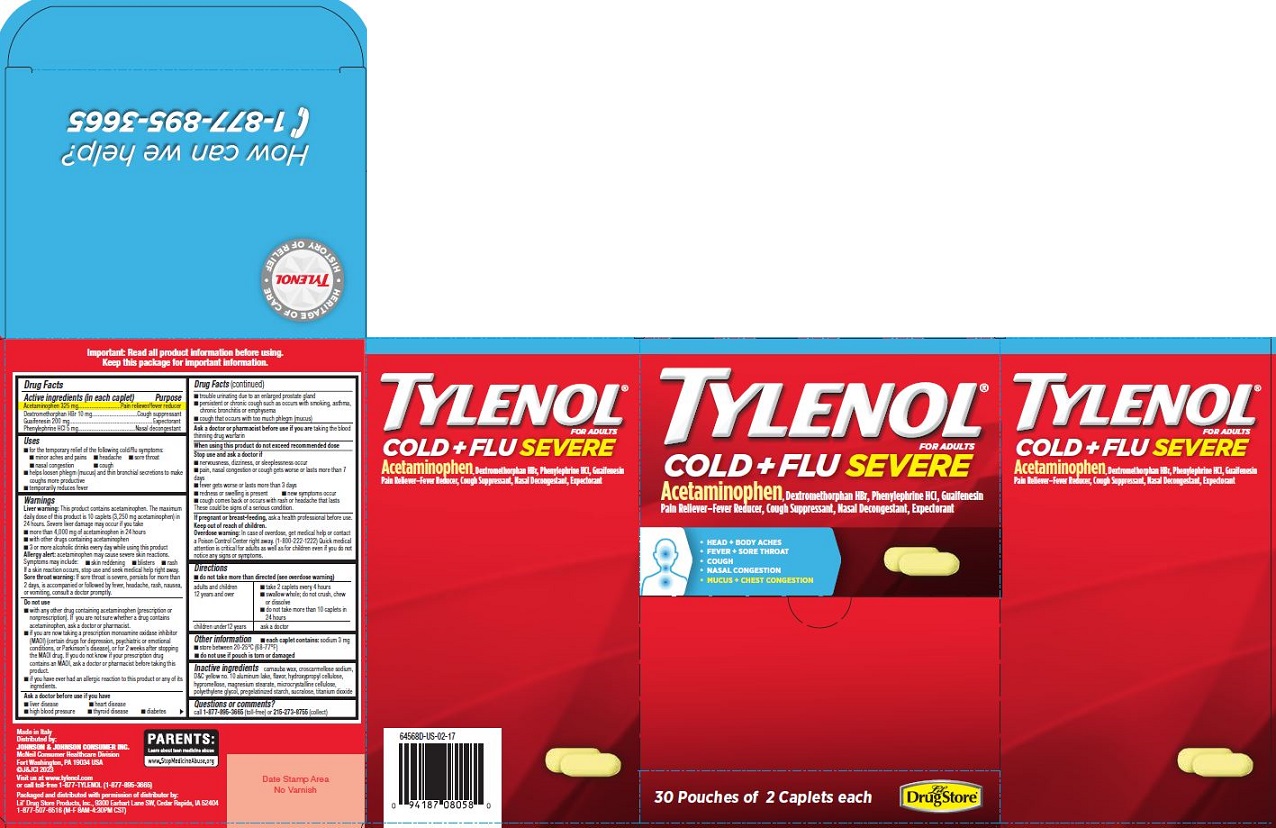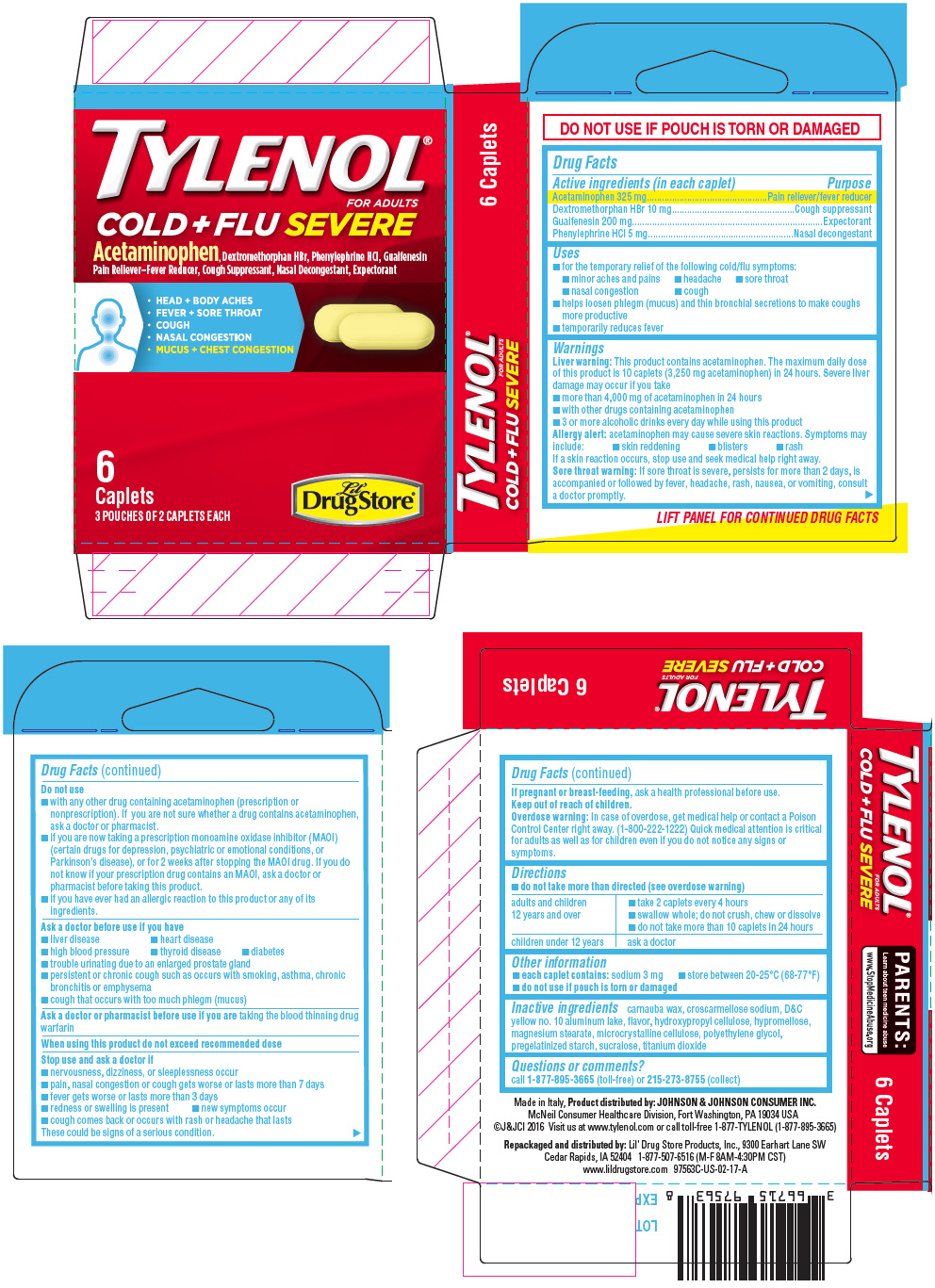 DRUG LABEL: Lil Drug Store Tylenol Cold plus Flu Severe
NDC: 66715-9756 | Form: TABLET, FILM COATED
Manufacturer: Lil Drug Store Products, Inc
Category: otc | Type: HUMAN OTC DRUG LABEL
Date: 20251210

ACTIVE INGREDIENTS: ACETAMINOPHEN 325 mg/1 1; DEXTROMETHORPHAN HYDROBROMIDE 10 mg/1 1; GUAIFENESIN 200 mg/1 1; PHENYLEPHRINE HYDROCHLORIDE 5 mg/1 1
INACTIVE INGREDIENTS: CROSCARMELLOSE SODIUM; D&C YELLOW NO. 10; ALUMINUM OXIDE; HYDROXYPROPYL CELLULOSE (70000 WAMW); HYPROMELLOSE, UNSPECIFIED; MAGNESIUM STEARATE; CARNAUBA WAX; MICROCRYSTALLINE CELLULOSE; POLYETHYLENE GLYCOL, UNSPECIFIED; STARCH, CORN; SUCRALOSE; TITANIUM DIOXIDE

Tylenol® Cold + Flu Severe,
Lil' Drug Store®, CVP® HEALTH, TRAVEL BASIX

Drug Facts

ACTIVE INGREDIENT

Active ingredients (in each caplet) | Purpose
Acetaminophen 325 mg | Pain reliever/fever reducer
Dextromethorphan HBr 10 mg | Cough suppressant
Guaifenesin 200 mg | Expectorant
Phenylephrine HCl 5 mg | Nasal decongestant

Uses

- for the temporary relief of the following cold/flu symptoms:
  - minor aches and pains
  - headache
  - sore throat
  - nasal congestion
  - cough
- helps loosen phlegm (mucus) and thin bronchial secretions to make coughs more productive
- temporarily reduces fever

Warnings

Liver warning

This product contains acetaminophen. The maximum daily dose of this product is 10 caplets (3,250 mg acetaminophen) in 24 hours. Severe liver damage may occur if you take

- more than 4,000 mg of acetaminophen in 24 hours
- with other drugs containing acetaminophen
- 3 or more alcoholic drinks every day while using this product

Allergy alert: acetaminophen may cause severe skin reactions. Symptoms may include:

- skin reddening
- blisters
- rash

If a skin reaction occurs, stop use and seek medical help right away.

Sore throat warning

If sore throat is severe, persists for more than 2 days, is accompanied or followed by fever, headache, rash, nausea, or vomiting, consult a doctor promptly.

Do not use

- with any other drug containing acetaminophen (prescription or nonprescription). If you are not sure whether a drug contains acetaminophen, ask a doctor or pharmacist.
- if you are now taking a prescription monoamine oxidase inhibitor (MAOI) (certain drugs for depression, psychiatric or emotional conditions, or Parkinson's disease), or for 2 weeks after stopping the MAOI drug. If you do not know if your prescription drug contains an MAOI, ask a doctor or pharmacist before taking this product.
- if you have ever had an allergic reaction to this product or any of its ingredients.

Ask a doctor before use if you have

- liver disease
- heart disease
- high blood pressure
- thyroid disease
- diabetes
- trouble urinating due to an enlarged prostate gland
- persistent or chronic cough such as occurs with smoking, asthma, chronic bronchitis or emphysema
- cough that occurs with too much phlegm (mucus)

Ask a doctor or pharmacist before use if you are taking the blood thinning drug warfarin

When using this product do not exceed recommended dose

Stop use and ask a doctor if

- nervousness, dizziness, or sleeplessness occur
- pain, nasal congestion or cough gets worse or lasts more than 7 days
- fever gets worse or lasts more than 3 days
- redness or swelling is present
- new symptoms occur
- cough comes back or occurs with rash or headache that lasts

These could be signs of a serious condition.

PREGNANCY OR BREAST FEEDING

If pregnant or breast-feeding, ask a health professional before use.

Keep out of reach of children.

Overdose warning

In case of overdose, get medical help or contact a Poison Control Center right away. (1-800-222-1222) Quick medical attention is critical for adults as well as for children even if you do not notice any signs or symptoms.

Directions

- do not take more than directed (see overdose warning)

adults and children 12 years and over | - take 2 caplets every 4 hours - swallow whole; do not crush, chew or dissolve - do not take more than 10 caplets in 24 hours
children under 12 years | ask a doctor

Other information

- each caplet contains: sodium 3 mg
- store between 20-25°C (68-77°F)
- do not use if pouch is torn or damaged

Inactive ingredients

carnauba wax, croscarmellose sodium, D&C yellow no. 10 aluminum lake, flavor, hydroxypropyl cellulose, hypromellose, magnesium stearate, microcrystalline cellulose, polyethylene glycol, pregelatinized starch, sucralose, titanium dioxide

Questions or comments?

call 1-877-895-3665 (toll-free) or 215-273-8755 (collect)

Product distributed by: JOHNSON & JOHNSON CONSUMER INC.
McNeil Consumer Healthcare Division, Fort Washington, PA 19034 USA

Repackaged and distributed by: Lil' Drug Store Products, Inc., 9300 Earhart Lane SW
Cedar Rapids, IA 52402

PRINCIPAL DISPLAY PANEL - 6 Caplet Pouch Carton

TYLENOL®
FOR ADULTS

COLD + FLU SEVERE

Acetaminophen, Dextromethorphan HBr, Phenylephrine HCl, Guaifenesin
Pain Reliever–Fever Reducer, Cough Suppressant, Nasal Decongestant, Expectorant

- HEAD + BODY ACHES
- FEVER + SORE THROAT
- COUGH
- NASAL CONGESTION
- MUCUS + CHEST CONGESTION

6
Caplets
3 POUCHES OF 2 CAPLETS EACH

Lil'
Drug Store®

Tylenol Cold + Flu SEVERE, CVP® Health 4ct - PDP/Package

TYLENOL®
FOR ADULTS

COLD + FLU SEVERE

Acetaminophen, Dextromethorphan HBr, Phenylephrine HCl, Guaifenesin
Pain Reliever–Fever Reducer, Cough Suppressant, Nasal Decongestant, Expectorant

HEAD + BODY ACHES
FEVER + SORE THROAT
COUGH
NASAL CONGESTION
MUCUS + CHEST CONGESTION

[caplets image]

4
Caplets
2 POUCHES OF 2 CAPLETS EACH

[CVP HEALTH logo]

Tylenol® Cold + Flu Severe, 25ct, Lil' Drug Store® - PDP/Package

TYLENOL®

FOR ADULTS

Cold + Flu Severe

Acetaminophen, Dextromethorphan HBr, Phenylephrine HCI, Guaifenesin
Pain Reliever–Fever Reducer, Cough Suppressant, Nasal Decongestant, Expectorant

- HEAD + BODY ACHES
- FEVER + SORE THROAT
- COUGH
- NASAL CONGESTION
- MUCUS + CHEST CONGESTION

[caplets (2) image]

25 Pouches of 2 Caplets each

[Lil' Drug Store logo]

Tylenol Cold + Flu SEVERE, TRAVEL BASIX 4ct - PDP/Package

TYLENOL®
FOR ADULTS

COLD + FLU SEVERE

Acetaminophen, Dextromethorphan HBr, Phenylephrine HCl, Guaifenesin
Pain Reliever–Fever Reducer, Cough Suppressant, Nasal Decongestant, Expectorant

HEAD + BODY ACHES
FEVER + SORE THROAT
COUGH
NASAL CONGESTION
MUCUS + CHEST CONGESTION

[caplets image]

4
Caplets
2 POUCHES OF 2 CAPLETS EACH

[TRAVEL BASIX logo]

Tylenol® Cold + Flu Severe, 30ct, Lil' Drug Store® - PDP/Package

TYLENOL®

FOR ADULTS

Cold + Flu Severe

Acetaminophen, Dextromethorphan HBr, Phenylephrine HCI, Guaifenesin
Pain Reliever–Fever Reducer, Cough Suppressant, Nasal Decongestant, Expectorant

- HEAD + BODY ACHES
- FEVER + SORE THROAT
- COUGH
- NASAL CONGESTION
- MUCUS + CHEST CONGESTION

[caplets (2) image]

30 Pouches of 2 Caplets each

[Lil' Drug Store® logo]